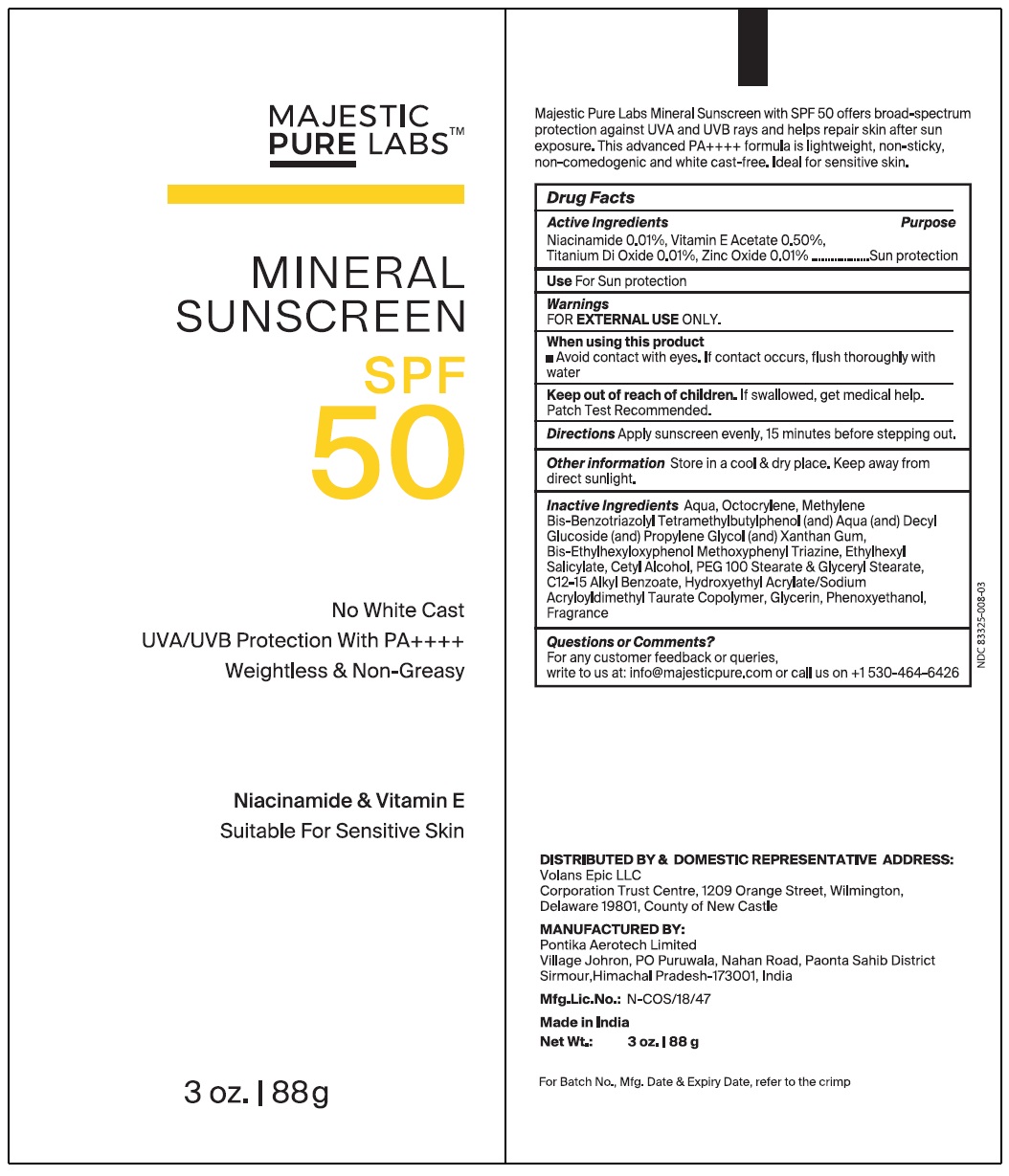 DRUG LABEL: MINERAL SUNSCREEN SPF 50
NDC: 83325-008 | Form: LOTION
Manufacturer: Volans Epic LLC
Category: otc | Type: HUMAN OTC DRUG LABEL
Date: 20240207

ACTIVE INGREDIENTS: NIACINAMIDE 0.1 g/88 g; .ALPHA.-TOCOPHEROL ACETATE 0.5 g/88 g; TITANIUM DIOXIDE 0.1 g/88 g; ZINC OXIDE 0.1 g/88 g
INACTIVE INGREDIENTS: WATER; OCTOCRYLENE; BISOCTRIZOLE; DECYL GLUCOSIDE; PROPYLENE GLYCOL; XANTHAN GUM; BEMOTRIZINOL; OCTISALATE; CETYL ALCOHOL; PEG-100 STEARATE; GLYCERYL MONOSTEARATE; ALKYL (C12-15) BENZOATE; HYDROXYETHYL ACRYLATE/SODIUM ACRYLOYLDIMETHYL TAURATE COPOLYMER (100000 MPA.S AT 1.5%); GLYCERIN; PHENOXYETHANOL; FRAGRANCE 13576

MINERAL SUNSCREEN SPF 50

INDICATIONS AND USAGE

No White Cast
UVA/UVB Protection With PA++++
Weightless & Non-Greasy
Niacinamide & Vitamin E
Suitable For Sensitive Skin

Active Ingredients Purpose

Niacinamide 0.01%, Vitamin E Acetate 0.50%, Titanium Di Oxide 0.01%, Zinc Oxide 0.01% ................. Sun protection

Use

For Sun protection

Warnings

FOR EXTERNAL USEONLY.

When using this product

■ Avoid contact with eyes. If contact occurs, flush thoroughly with water

KEEP OUT OF REACH OF CHILDREN

Keep out of reach or children.If swallowed, get medical help. Patch Test Recommended.

Directions

Apply sunscreen evenly, 15 minutes before stepping out.

Other lnformation

Store in a cool & dry place. Keep away from direct sunlight.

Inactive lngredlents

Aqua, Octocrylene, Methylene Bis-Benzotriazolyl Tetramethylbutylphenol (and) Aqua (and) Decyl Glucoslde (and) Propylene Glycol (and) Xanthan Gum, Bis-Ethylhexyloxyphenol Methoxyphenyl Triazine, Ethylhexyl Salicylate, Cetyl Alcohol, PEG 100 Stearate & Glyceryl Stearate, C12-15 Alkyl Benzoate, Hydroxyethyl Acrylate/Sodium Acryloyldimethyl Taurate Copolymer, Glycerin, Phenoxyethanol, Fragrance.

Questions or Comments?

For any customer feedback or queries, write to us at: info@majesticpure.com or call us on +1 530-464-6426

DISTRIBUTED BY & DOMESTIC REPRESENTATIVE ADDRESS:
Volans Epic LLC
Corporation Trust Center, 1209 Orange Street, Wilmington,
Delaware 19801, Country of New Castle

MANUFACTURED BY:
Pontika Aerotech Limited
Village Johron, PO Puruwala, Nahan Road, Paonta Sahib District
Sirmour, Himachal Pradesh-173001, India

Mfg.Lic.No.:N-COS/18/47

Made in India